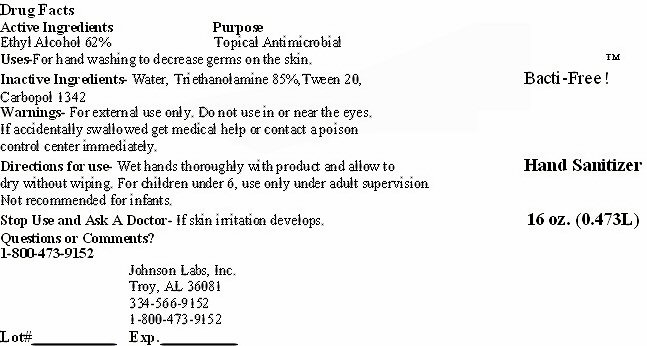 DRUG LABEL: Bacti-Free tm
NDC: 59854-299 | Form: LIQUID
Manufacturer: Johnson Labs, Inc.
Category: otc | Type: HUMAN OTC DRUG LABEL
Date: 20120402

ACTIVE INGREDIENTS: ALCOHOL 0.29326 L/0.473 L
INACTIVE INGREDIENTS: WATER; TROLAMINE; POLYSORBATE 20; CARBOMER 1342

Active Ingredients

Drug Facts

Active Ingredients Ethyl Alcohol 62%

Purpose

Purpose Topical Antimicrobial

Keep Out Of Reach Of Children

For children under 6, use only under adult supervision. Not recommended for infants. If accidentally swallowed get medical help or contact a poison control center immediately.

Uses

Uses - For hand washing to decrease germs on the skin.

Warnings

Warnings - For external use only. Do not use in or near the eyes. If accidentally swallowed get medical help or contact a poison control center immediately.

Directions for use - Wet hands throughly with product and allow to dry without wiping. For children under 6, use only under adult supervision.

Inactive Ingredients

Inactive Ingredients - Water, Triethanolamine 85%, Tween 20, Carbopol 1342

Stop use and ask a Doctor - If skin irritation develops.

Questions or Comments?

1-800- 473-9152

Bacti-Free tm Label

Bacti-Free! tm Hand Sanitizer

16 oz. (0.473L)

Johnson Labs, Inc Troy, AL 36081 334-566-9152 1-800-473-9152

Lot # __________ Exp. ___________